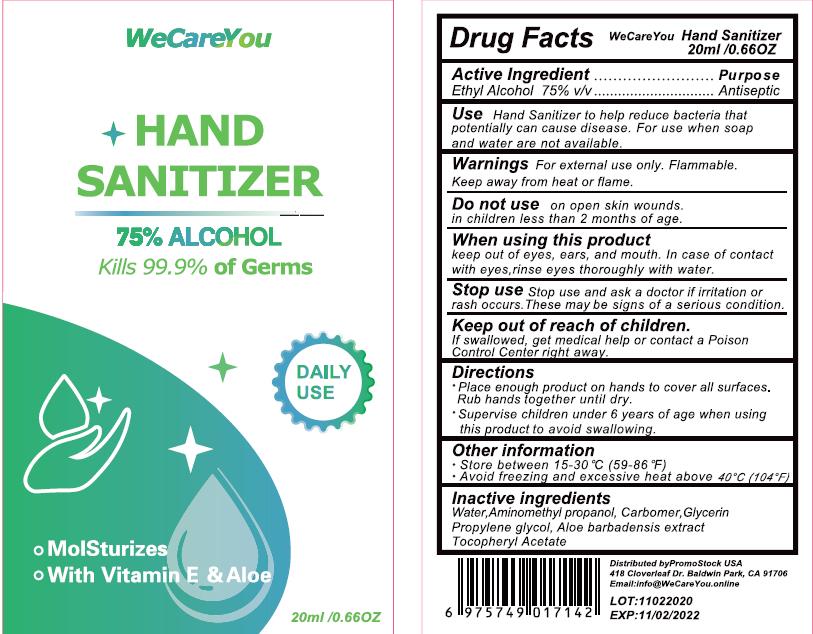 DRUG LABEL: HAND SANITIZER
NDC: 75749-052 | Form: GEL
Manufacturer: NINGBO PRETTY TOURISM MANUFACTURE CO.,LTD.
Category: otc | Type: HUMAN OTC DRUG LABEL
Date: 20201102

ACTIVE INGREDIENTS: ALCOHOL 75 mL/100 mL
INACTIVE INGREDIENTS: 1,2-PROPANEDIOL, 1-BENZOATE; ALOE VERA LEAF; WATER; AMINOMETHYLPROPANOL; .ALPHA.-TOCOPHEROL ACETATE; CARBOMER HOMOPOLYMER, UNSPECIFIED TYPE; GLYCERIN

Active Ingredient

Ethyl Alcohol 75%v/v

Purpose

Antiseptic

Use

Hand Sanitizer to help reduce bacteria that potentially can cause disease. For use when soap and water are not available.

Warnings

For external use only. Flammable. Keep away from heat or flame.

Do not use on open skin wounds. in children less than 2 mouths of age.

When using this product, keep out of eyes, ears and mouth. In case of contact with eyes, rinse eyes thoroughly with water.

Stop use

Stop ue and ask a doctor if irritation or rash occurs. These may be signs of a serious condition.

Keep out of reach of children

If swallowed, get medical help or contact a Poison Control Center right away.

Directions

- Place enough product on hands to cover all surfaces. Rub hands together until dry.
- Supervise children under 6 years of age when using this product to avoid swallowing.

Other information

- Store between 15-30C (59-86F)
- Avoid freezing and excessive heat above 40C (104F)

Inactive ingredients

Water ,

Aminomethyl propanol ,

Carbomer ,

Glycerin,

Propylene glycol ,

Aloe barbadensis extract ,

Tocopheryl Acetate